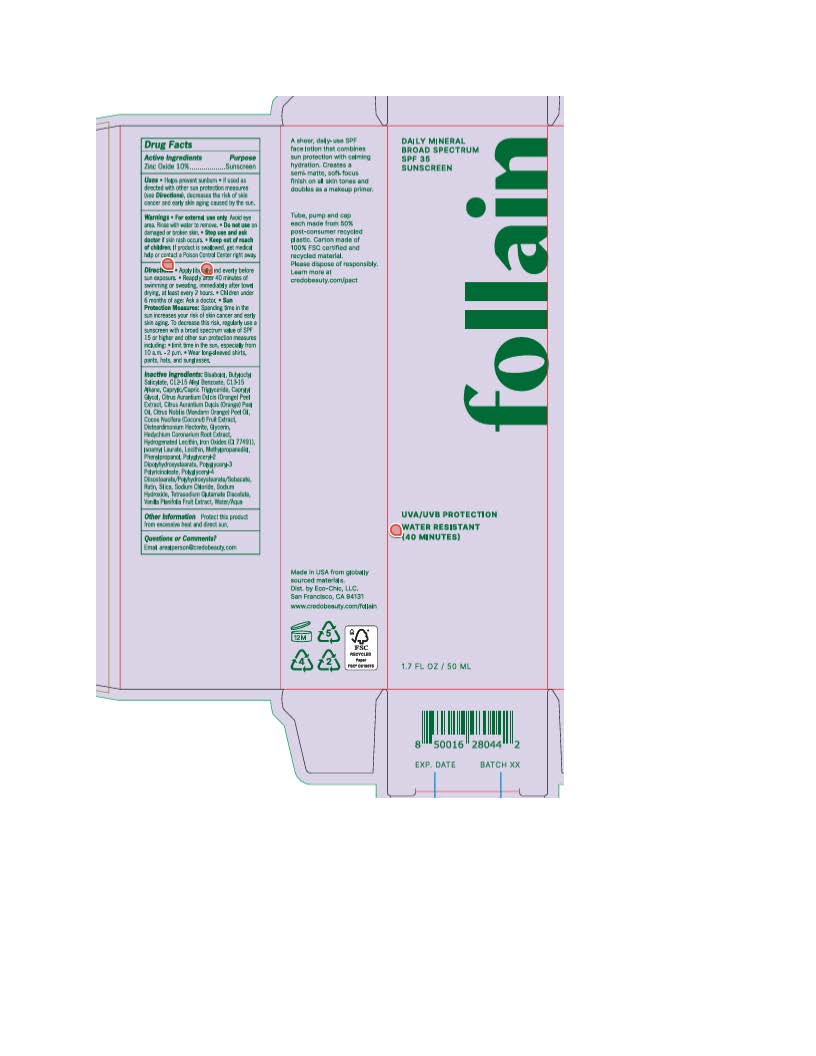 DRUG LABEL: Credo Follain Daily Mineral Sunscreen
NDC: 79163-138 | Form: LOTION
Manufacturer: Eco-Chic LLC
Category: otc | Type: HUMAN OTC DRUG LABEL
Date: 20251117

ACTIVE INGREDIENTS: ZINC OXIDE 110 mg/1 mL
INACTIVE INGREDIENTS: BUTYLOCTYL SALICYLATE; DISTEARDIMONIUM HECTORITE; RUTIN; GLYCERIN; ISOAMYL LAURATE; FERRIC OXIDE YELLOW; SILICON DIOXIDE; TOCOPHEROL; CAPRYLYL GLYCOL; PHENYLPROPANOL; LECITHIN, SOYBEAN; METHYLPROPANEDIOL; POLYGLYCERYL-2 DIPOLYHYDROXYSTEARATE; ALLANTOIN; ALKYL (C12-15) BENZOATE; .ALPHA.-BISABOLOL, (+)-; WATER; SODIUM CHLORIDE; HYDROGENATED SOYBEAN LECITHIN; FERRIC OXIDE RED; FERROSOFERRIC OXIDE; C13-15 ALKANE; POLYGLYCERYL-3 RICINOLEATE; POLYGLYCERYL-4 DIISOSTEARATE/POLYHYDROXYSTEARATE/SEBACATE

Credo Follain Daily Mineral Sunscreen